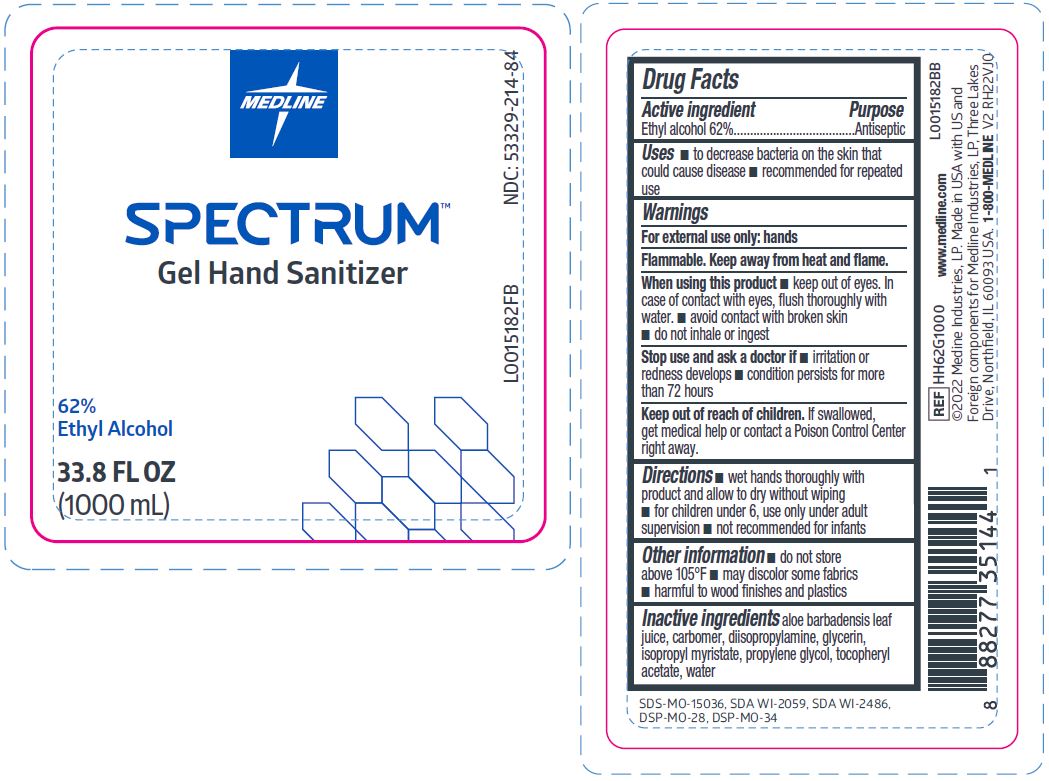 DRUG LABEL: Spectrum 62% Hand Sanitizer
NDC: 53329-214 | Form: GEL
Manufacturer: Medline Industries, LP
Category: otc | Type: HUMAN OTC DRUG LABEL
Date: 20260211

ACTIVE INGREDIENTS: ALCOHOL 62 mL/100 mL
INACTIVE INGREDIENTS: GLYCERIN; .ALPHA.-TOCOPHEROL ACETATE, D-; CARBOMER HOMOPOLYMER, UNSPECIFIED TYPE; DIISOPROPYLAMINE; ISOPROPYL MYRISTATE; PROPYLENE GLYCOL; WATER; ALOE VERA LEAF

214 Spectrum 62% Hand Sanitizer

Active ingredient

Ethyl alcohol 62% v/v

Purpose

Antiseptic

Uses

- to decrease bacteria on the skin that could cause disease
- recommended for repeated use

Warnings

For external use only: hands

Flammable. Keep away from heat and flame.

When using this product

- keep out of eyes. In case of contact with eyes, flush thoroughly with water
- avoid contact with broken skin
- do not inhale or ingest

Stop use and ask a doctor if

- irritation or redness develops
- condition persists for more than 72 hours

Keep out of reach of children.

If swallowed, get medical help or contact a Poison Control Center right away.

Directions

- wet hands thoroughly with product and allow to dry without wiping
- for children under 6, use onlyunder adult supervision
- not recommended for infants

Other information

- do not store above 105°F
- may discolor some fabrics
- harmful to wood finishes and plastics

Inactive ingredients

aloe barbadensis leaf juice, carbomer, diisopropylamine, glycerin, isopropyl myristate, propylene glycol, tocopheryl acetate, water

Manufacturing Information

Manufactured for:

Medline Industries, LP

Three Lakes Drive, Northfield, IL 60093 USA

Made in USA with US and foreign components

www.medline.com

1-800-MEDLINE (633-5463)

REF: HH62G1000

V2 RH22VJO